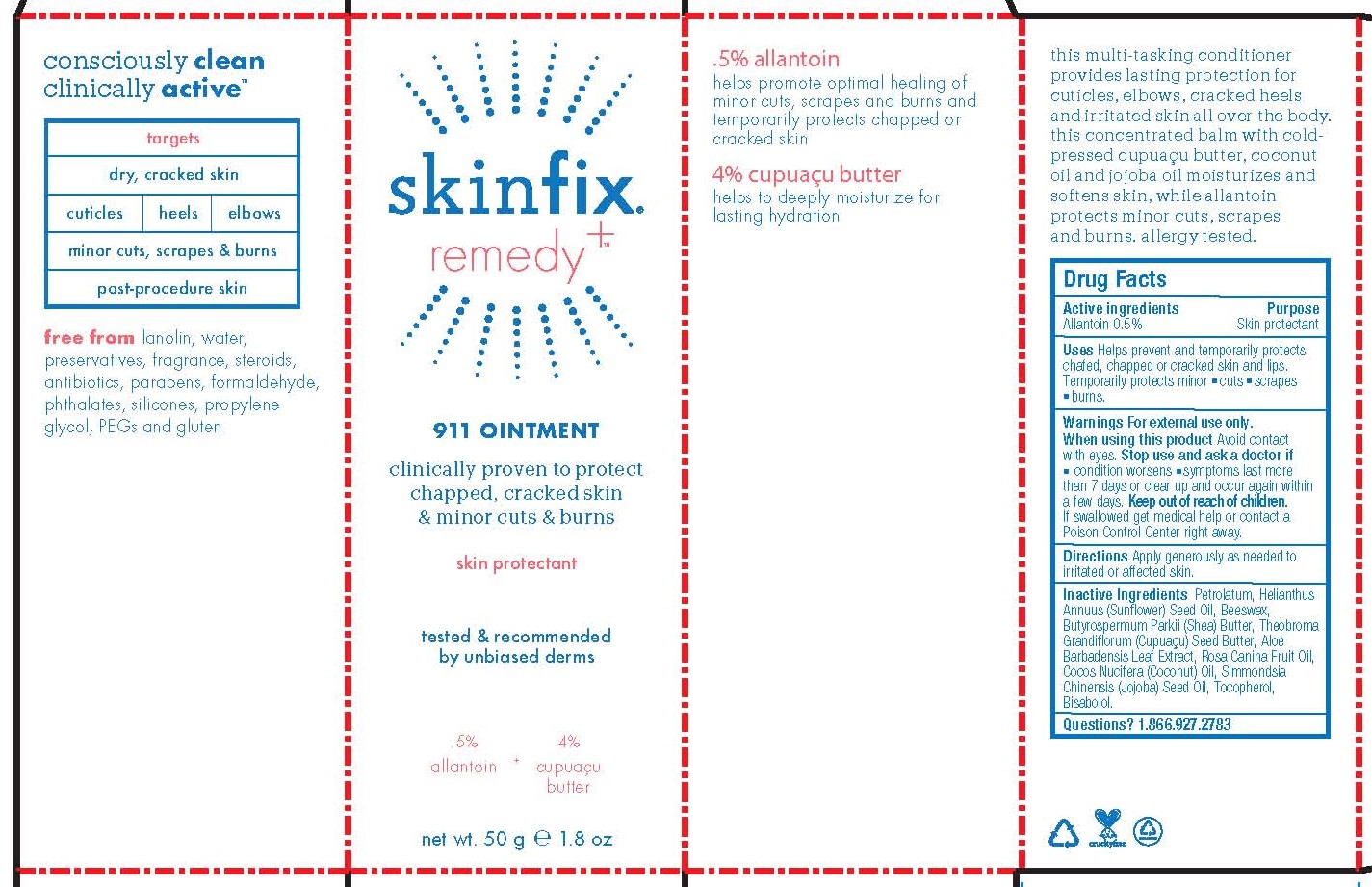 DRUG LABEL: 911
NDC: 61328-120 | Form: OINTMENT
Manufacturer: Skinfix, Inc.
Category: otc | Type: HUMAN OTC DRUG LABEL
Date: 20251229

ACTIVE INGREDIENTS: ALLANTOIN 0.5 g/100 g
INACTIVE INGREDIENTS: ALOE VERA LEAF; YELLOW WAX; LEVOMENOL; SHEANUT OIL; COCONUT OIL; THEOBROMA GRANDIFLORUM SEED BUTTER; SUNFLOWER OIL; PETROLATUM; ROSA CANINA FRUIT OIL; JOJOBA OIL; TOCOPHEROL

SKINFIX - 911 OINTMENT (61328-120)

Active Ingredients

Allantoin 0.5%

Purpose

Skin protectant

Uses

Restores and protects lips, cuticles and dry patches.

Warnings

For external use only.

When using this product

- Avoid contact with eyes

KEEP OUT OF REACH OF CHILDREN.

Directions

Apply as needed.

Inactive Ingredients

Aloe Barbadensis Leaf Extract, Beeswax, Bisabolol, Butyrospermum Parkii (Shea) Butter, Cocos Nucifera (Coconut) Oil, Cupuacu (Theobroma Grandiflorum) Seed Butter, Helianthus Annuus (Sunflower) Seed Oil, Petrolatum, Rosa Canina Fruit Oil, Simmondsia Chinensis (Jojoba) Seed Oil, Tocopherol.